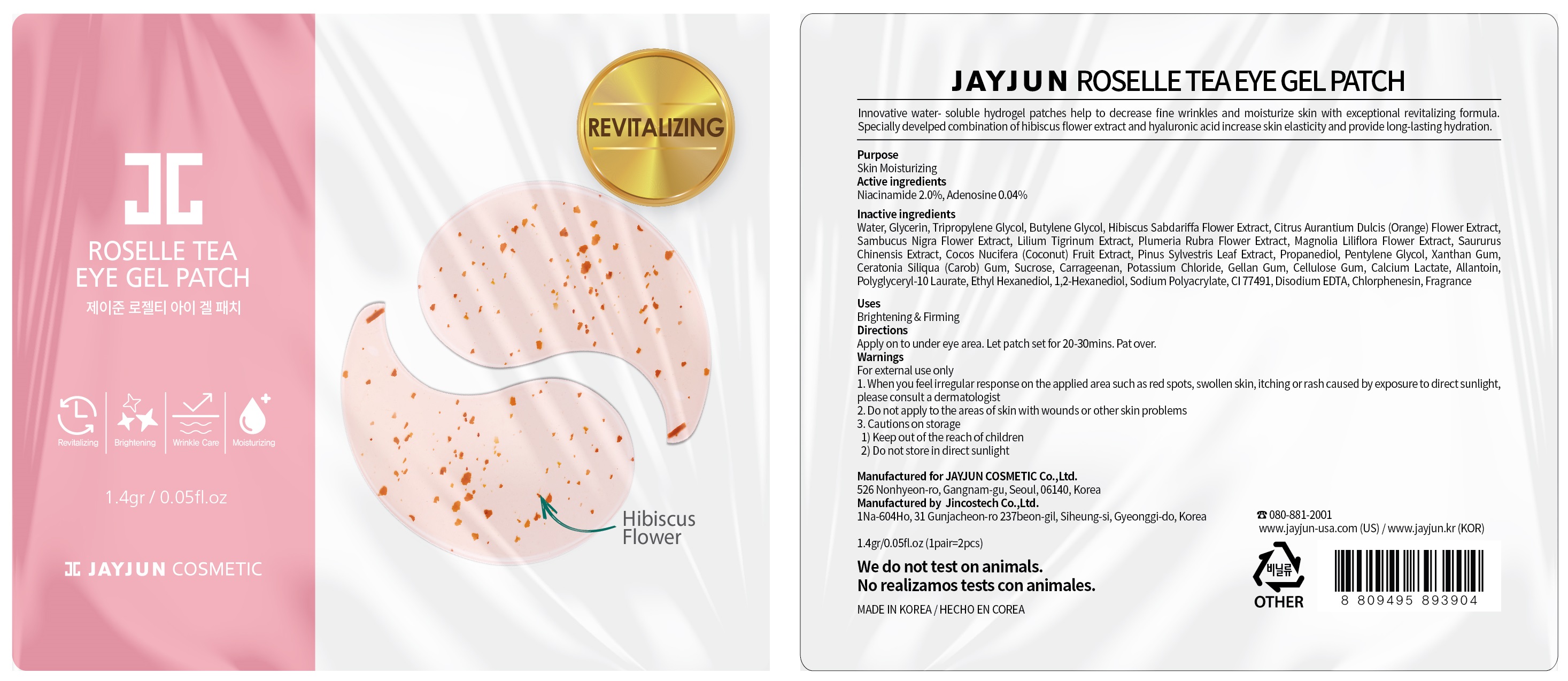 DRUG LABEL: ROSELLE TEA EYE GE L
NDC: 70920-680 | Form: PATCH
Manufacturer: JAYJUN COSMETIC Co.,Ltd.
Category: otc | Type: HUMAN OTC DRUG LABEL
Date: 20190218

ACTIVE INGREDIENTS: Niacinamide 0.028 g/1.4 g; Adenosine 0.0005 g/1.4 g
INACTIVE INGREDIENTS: Water; Glycerin

ACTIVE INGREDIENT

Active ingredients: Niacinamide 2.0%, Adenosine 0.04%

INACTIVE INGREDIENT

Inactive ingredients
■ Water, Glycerin, Tripropylene Glycol, Butylene Glycol, Hibiscus Sabdariffa Flower Extract, Citrus Aurantium Dulcis (Orange) Flower Extract, Sambucus Nigra Flower Extract, Lilium Tigrinum Extract, Plumeria Rubra Flower Extract, Magnolia Liliflora Flower Extract, Saururus Chinensis Extract, Cocos Nucifera (Coconut) Fruit Extract, Pinus Sylvestris Leaf Extract, Propanediol, Pentylene Glycol, Xanthan Gum, Ceratonia Siliqua (Carob) Gum, Sucrose, Carrageenan, Potassium Chloride, Gellan Gum, Cellulose Gum, Calcium Lactate, Allantoin, Polyglyceryl-10 Laurate, Ethyl Hexanediol, 1,2-Hexanediol, Sodium Polyacrylate, CI 77491, Disodium EDTA, Chlorphenesin, Fragrance

PURPOSE

Purpose: Skin Moisturizing

WARNINGS

For external use only
1. When you feel irregular response on the applied area such as red spots, swollen skin, itching or rash caused by exposure to direct sunlight, please consult a dermatologist
2. Do not apply to the areas of skin with wounds or other skin problems
3. Cautions on storage
1) Keep out of the reach of children
2) Do not store in direct sunlight

KEEP OUT OF REACH OF CHILDREN

Uses

Brightening & Firming

Directions

Directions:Apply on to under eye area. Let patch set for 20-30mins. Pat over.